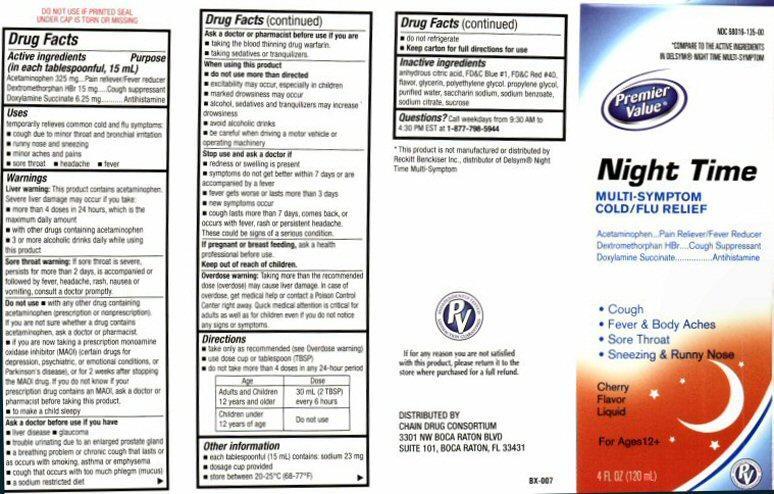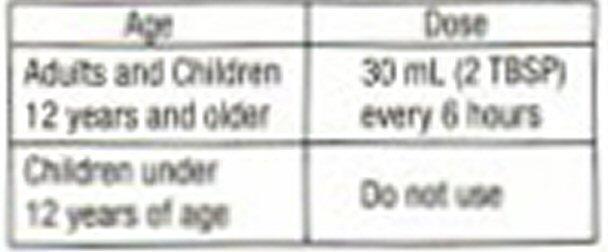 DRUG LABEL: Night Time
NDC: 68016-135 | Form: LIQUID
Manufacturer: Chain Drug Consortium, LLC
Category: otc | Type: HUMAN OTC DRUG LABEL
Date: 20130401

ACTIVE INGREDIENTS: ACETAMINOPHEN 325 mg/15 mL; DEXTROMETHORPHAN HYDROBROMIDE 15 mg/15 mL; DOXYLAMINE SUCCINATE 6.25 mg/15 mL
INACTIVE INGREDIENTS: CITRIC ACID MONOHYDRATE; FD&C BLUE NO. 1; FD&C RED NO. 40; GLYCERIN; POLYETHYLENE GLYCOL 400; PROPYLENE GLYCOL; WATER; SACCHARIN SODIUM; SODIUM BENZOATE; SODIUM CITRATE; SUCROSE

Active ingredients

Drug Facts
Active ingredients (in each tablespoonful, 15 mL)
Acetaminophen 325 mg
Dextromethorphan HBr 15 mg
Doxylamine Succinate 6.25 mg

Purpose

Pain reliever/fever reducer
Cough suppressant
Antihistamine

Keep out of reach of children

Uses

temporarily relieves cold/flu symptoms:

- cough due to minor sore throat and bronchial irritation
- runny nose and sneezing
- minor aches and pain
- sore throat
- headache
- fever

Warnings

Liver warning: This product contains acetaminophen. Severe liver damage may occur if you take:

- more than 4 doses in 24 hours, which is the maximum daily amount
- with other drugs containing acetaminophen
- 3 or more alcoholic drinks every day while using this product.

Sore throat warning: If sore throat is severe, persists for more than 2 days, is accompanied or followed by fever, headache, rash, nausea, or vomiting, consult a doctor promptly.

Do not use

- with any other drug containing acetaminophen (prescription or nonprescription) If you are not sure whether a drug contains acetaminophen, ask a doctor or pharmacist
- if you are now taking a prescription monoamine oxidase inhibitor (MAOI) (certain drugs for depression,psychiatric or emotional conditions, or Parkinson's disease), or for 2 weeks after stopping the MAOI drug. If you do not know if your prescription drug contains an MAOI, ask a doctor or pharmacist before taking this product
- to make a child sleepy

Ask a doctor before use if you have

- liver disease
- glaucoma
- trouble urinating due to enlarged prostate gland
- a breathing problem or chronic cough that lasts or as occurs with smoking, asthma, chronic bronchitis or emphysema
- cough that occurs with too much phlegm (mucus)
- a sodium restricted diet

Ask a doctor or pharmacist before use

- if you are taking the blood thinning drug warfarin
- if you are taking sedatives or tranquilizers

When using this product

- do not use more than directed

- excitability may occur, especially in children
- marked drowsiness may occur
- alcohol, sedatives, and tranquilizers may increase drowsiness
- avoid alcoholic drinks
- be careful when driving a motor vehicle or operating machinery

Stop use and ask a doctor if

- redness or swelling is present
- symptoms do not get better within 7 days or are accompanied by a fever
- fever gets worse or lasts more than 3 days
- new symptoms occur
- cough lasts more than 7 days, comes back, or occurs with fever, rash, or persistent headache.

- These could be signs of a serious condition.

If pregnant or breast-feeding

ask a health professional before use.

Overdose warning

Taking more than the recommended dose (overdose) may cause liver damage. In case of overdose, get medical help or contact a Poison Control Center right away. Quick medical attention is critical for adults as well as for children even if you do not notice any signs or symptoms.

Directions

- take only as recommended (see Overdose warning)
- use dose cup or tablespoon (TBSP)
- do not take more than 4 doses in any 24-hours

Other information

- each tablespoonful (15 mL) contains: sodium 23 mg
- dosage cup provided
- store between 20-25° C (68-77° F)
- do not refrigerate
- Keep carton for full directions for use

Inactive ingredients

anhydrous citric acid, FD and C Blue No. 1, FD and C Red No. 40, flavor, glycerin, polyethylene glycol, propylene glycol, purified water, saccharin sodium, sodium benzoate, sodium citrate, sucrose

Questions?

Call weekdays from 9:30 AM to 4:30 PM EST at
1-877-798-5944

Product Label

NDC 68016-135-00
COMPARE TO THE ACTIVE INGREDIENTS IN DELSYM® NIGHT TIME MULTI-SYMPTOM
Premier Value®
Night Time
MULTI-SYMPTOM COLD/FLU RELIEF
Acetaminophen……Pain Reliever/Fever Reducer
Dextromethorphan HBr……Cough Suppressant
Doxylamine Succinate ……………Antihistamine
Cough
Fever and Body Aches
Sore Throat
Sneezing and Runny Nose
Cherry Flavored Liquid
For Ages 12 +
4 FL OZ (120 mL)
INDEPENDENTLY TESTED SATISFACTION GUARANTEED PV
DO NOT USE IF PRINTED SEAL UNDER CAP IS TORN OR MISSING
*This product is not manufactured or distributed by Reckitt Benckiser Inc.,Distributor of Delsym® Night Time Multi-Symptom
If for any reason you are not satisfied with this product, please return it to the store where purchased for a full refund.
DISTRIBUTED BY
CHAN DRUG CONSORTIUM
3301 NW BOCO RATON BLVD
SUITE 101, BOCA RATON FL 33431
BX-007